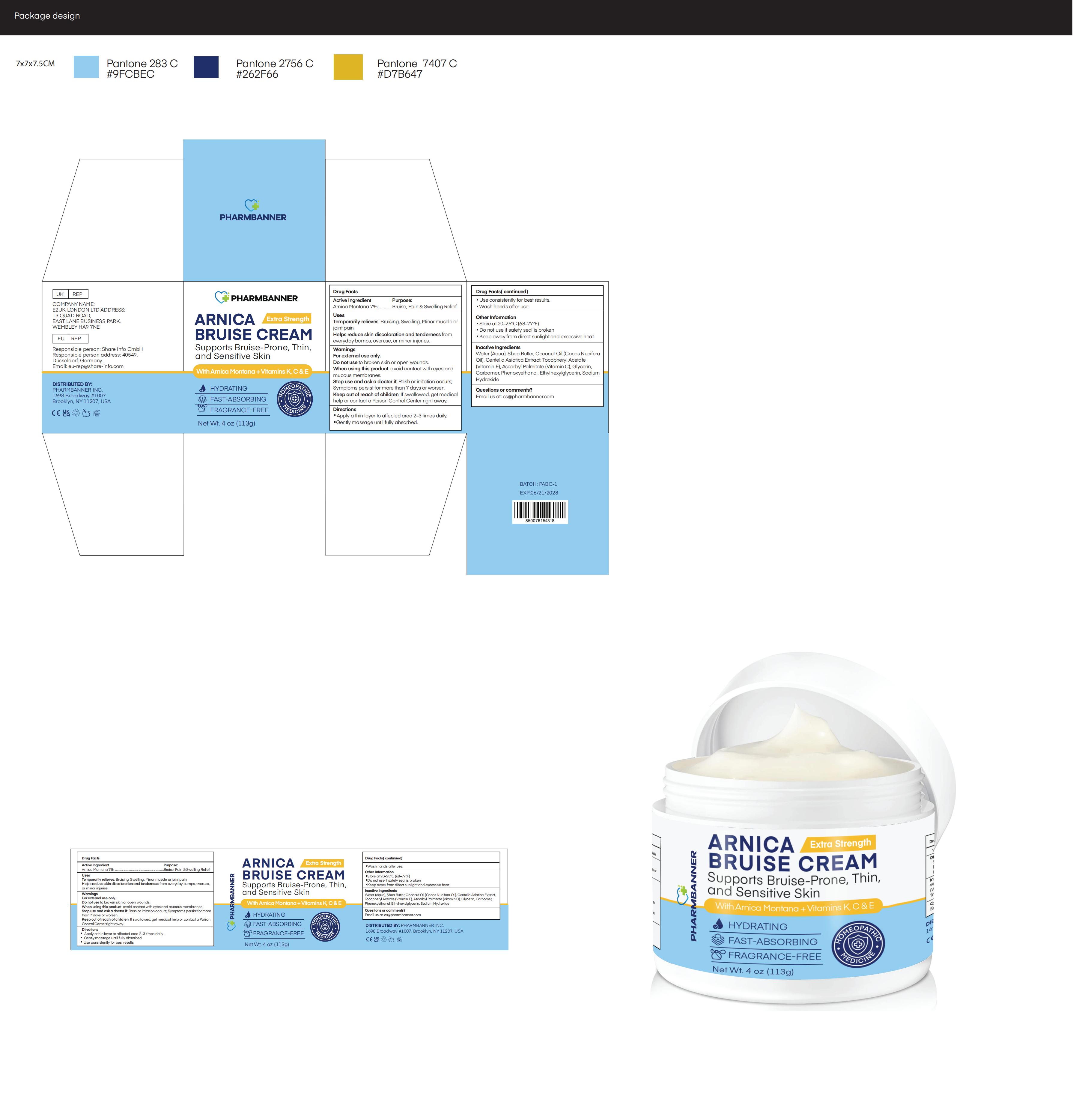 DRUG LABEL: PHARMBANNER Arnica Bruise Cream
NDC: 83818-023 | Form: CREAM
Manufacturer: Shenzhen Xinxin Yunhai Technology Co., Ltd.
Category: otc | Type: HUMAN OTC DRUG LABEL
Date: 20260212

ACTIVE INGREDIENTS: CLOTRIMAZOLE 7 g/100 g
INACTIVE INGREDIENTS: ETHYLHEXYLGLYCERIN; COCOS NUCIFERA (COCONUT) OIL; .ALPHA.-TOCOPHEROL ACETATE; SHEA BUTTER; ASCORBYL PALMITATE; GLYCERIN; PHENOXYETHANOL; SODIUM HYDROXIDE; WATER; CENTELLA ASIATICA TRITERPENOIDS; CARBOMER

83818-023 Update Manufacturer

Active Ingredient

Arnica Montana 7%

Purpose

Bruise, Pain & Swelling Relief

Use

Temporarily relieves: Bruising, Swelling, Minor muscle or joint pain.
Helps reduce skin discoloration and tenderness from
everyday bumps, overuse, or minor injuries.

Warnings

For external use only.

Do not use

to broken skin or open wounds.

When Using

avoid contact with eyes and mucous membranes.

Stop Use

Rash or irritation occurs;
Symptoms persist for more than 7 days or worsen.

Ask Doctor

Rash or irritation occurs;
Symptoms persist for more than 7 days or worsen.

Keep Out Of Reach Of Children

If swallowed, get medical help or contact a Poison Control Center right away.

Directions

■ Apply a thin layer to affected area 2–3 times daily.
■ Gently massage until fully absorbed.
■ Use consistently for best results.
■ Wash hands after use.

Other information

■ Store at 20–25°C (68–77°F)
■ Do not use if safety seal is broken
■ Keep away from direct sunlight and excessive heat

Inactive ingredients

Water (Aqua), Shea Butter, Coconut Oil (Cocos NuciferaOil), Centella Asiatica Extract, Tocopheryl Acetate
(Vitamin E), Ascorbyl Palmitate (Vitamin C), Glycerin, Carbomer, Phenoxyethanol, Ethylhexylglycerin, Sodium Hydroxide

Questions

Email us at: cs@pharmbanner.com